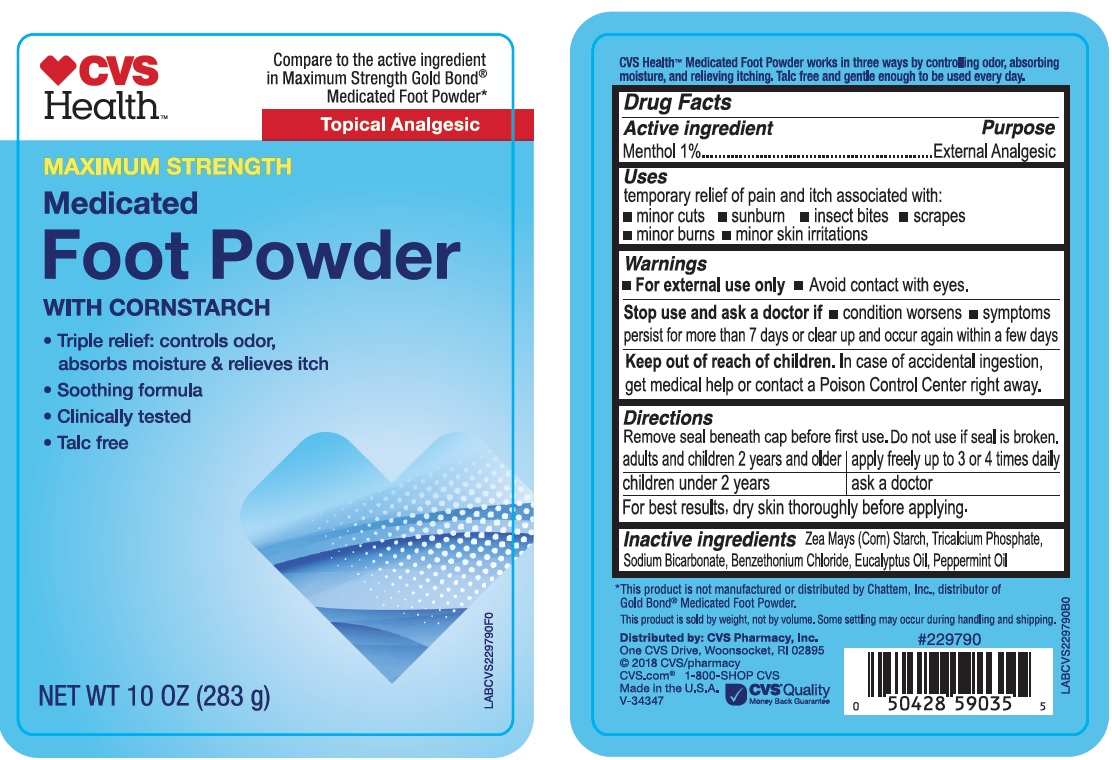 DRUG LABEL: Maximum Strength Medicated Foot Powder
NDC: 42669-283 | Form: POWDER
Manufacturer: Davion, Inc
Category: otc | Type: HUMAN OTC DRUG LABEL
Date: 20251229

ACTIVE INGREDIENTS: MENTHOL 1 g/100 g
INACTIVE INGREDIENTS: STARCH, CORN; TRICALCIUM PHOSPHATE; SODIUM BICARBONATE; EUCALYPTUS OIL; BENZETHONIUM CHLORIDE; PEPPERMINT OIL

MAXIMUM STRENGTH Medicated Foot Powder with Corn Starch

Active Ingredient

Menthol 1.0%

Purpose

External Analgesic

Uses

Temporary relief of pain and itch associated with:

- minor cuts
- sunburn
- insect bites
- scrapes
- minor burns
- minor skin irritations

Warning

- For external use only
- Avoid contact with eyes

Stop use and ask a doctor if

- condition worsens
- symptoms persist for more than 7 days or clear up and occur again within few days

Keep out of reach of children

In case of accidental ingestion, get medical help or contact a poison control center right away.

Directions

Remove seal beneath cap before first use. Do not use if seal is broken

- adults and children 2 years and older - apply freely upto 3 or 4 times daily
- children under 2 years - ask a doctor

For best results, dry skin throughly before applying

Inactive ingredients

Zea Mays (Corn) Starch, Tricalcium Phosphate, Sodium Bicarbonate, Benzethonium Chloride, Eucalyptus Oil, Peppermint Oil

PRINCIPAL DISPLAY PANEL

NDC 42669-283-01

CVS HEALTH Compared to the active ingredient in Maximum Strength Gold bond Medicated Foot Powder*

MAXIMUM STRENGTH Medicated Foot Powder WITH CORNSTARCG

- Triple Relief: controls odor, absorbs moisture & relieves itc
- Soothing formula
- Clinically tested
- Talc free

NET WT 10 OZ (283 g)